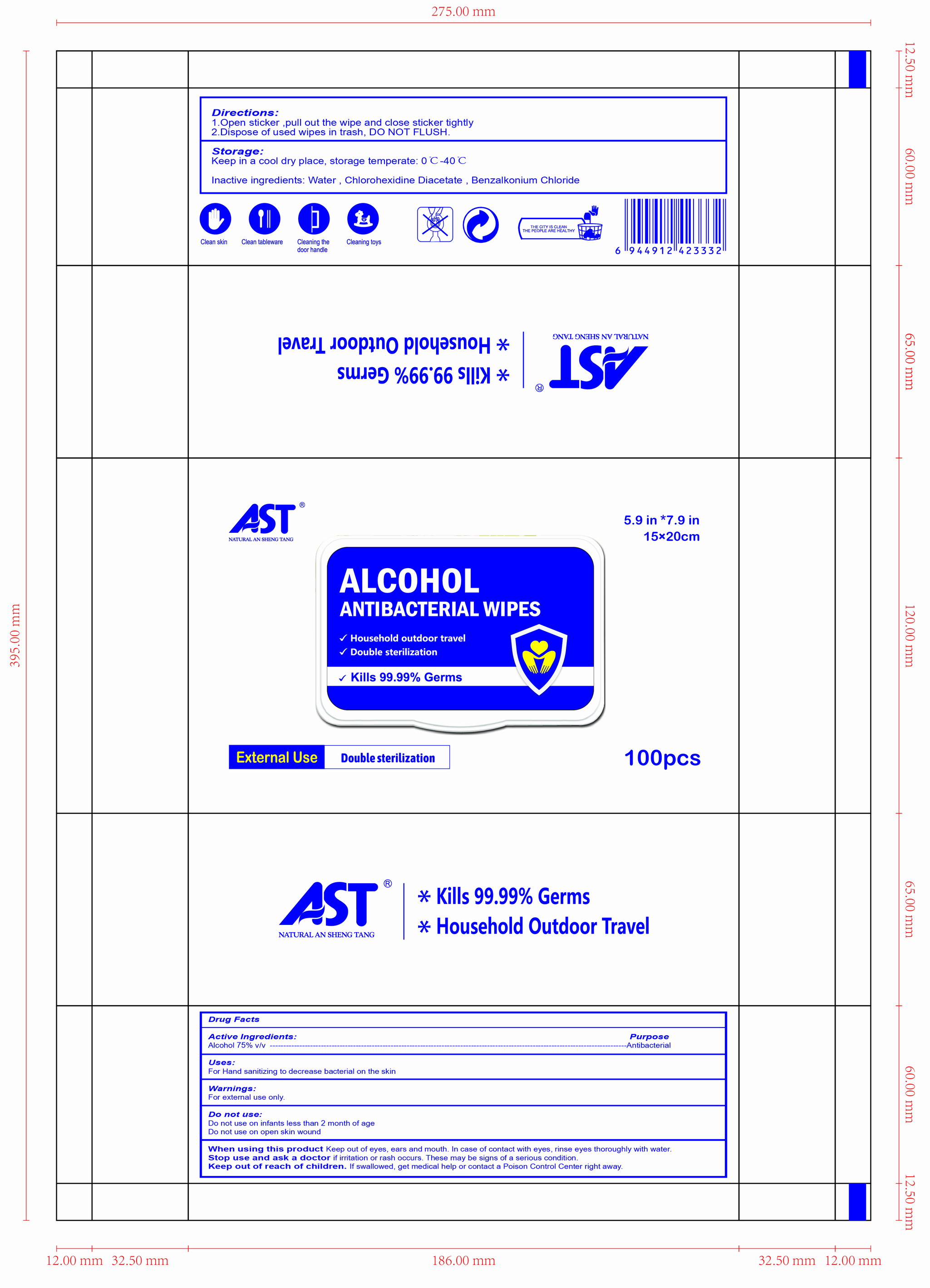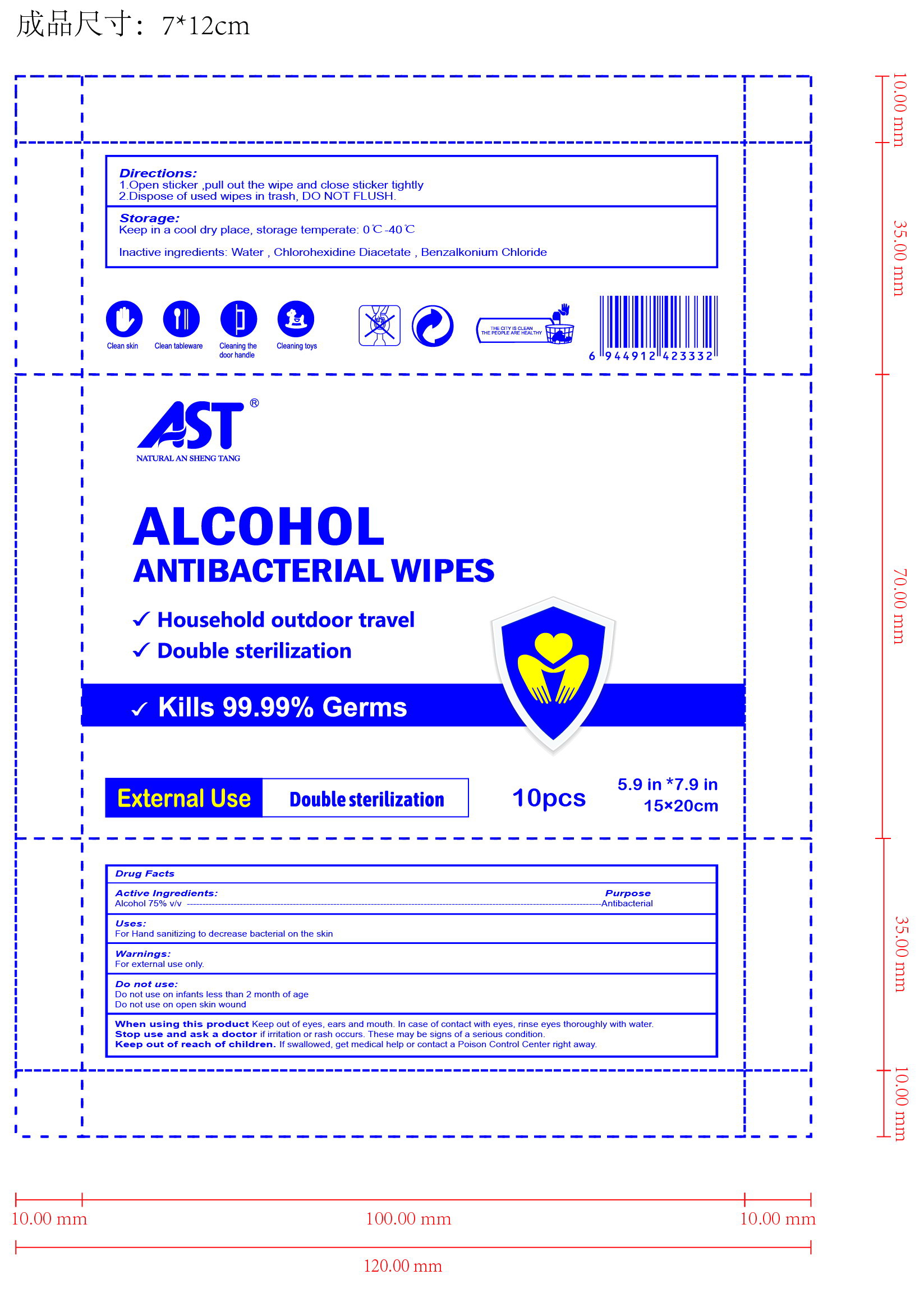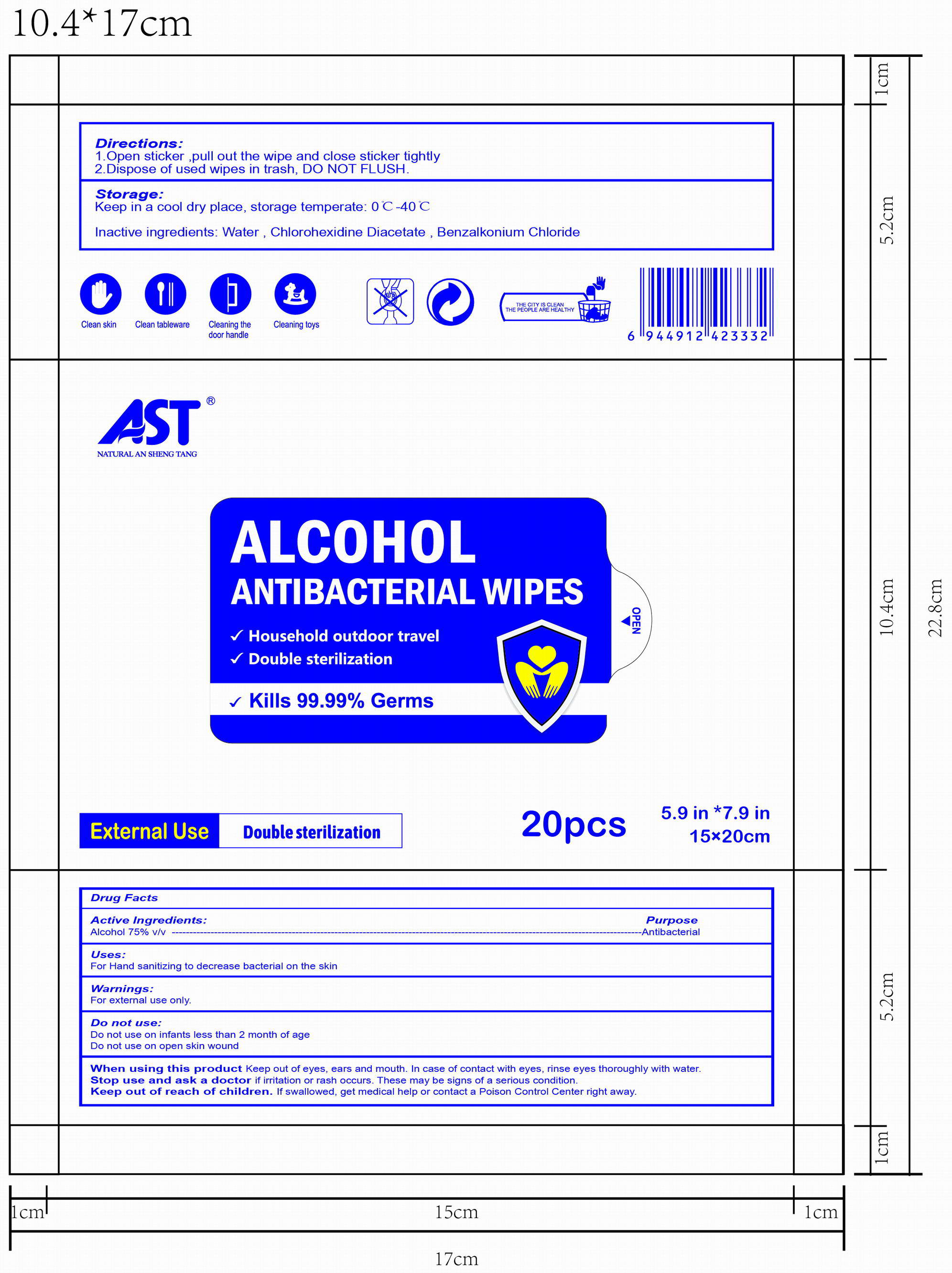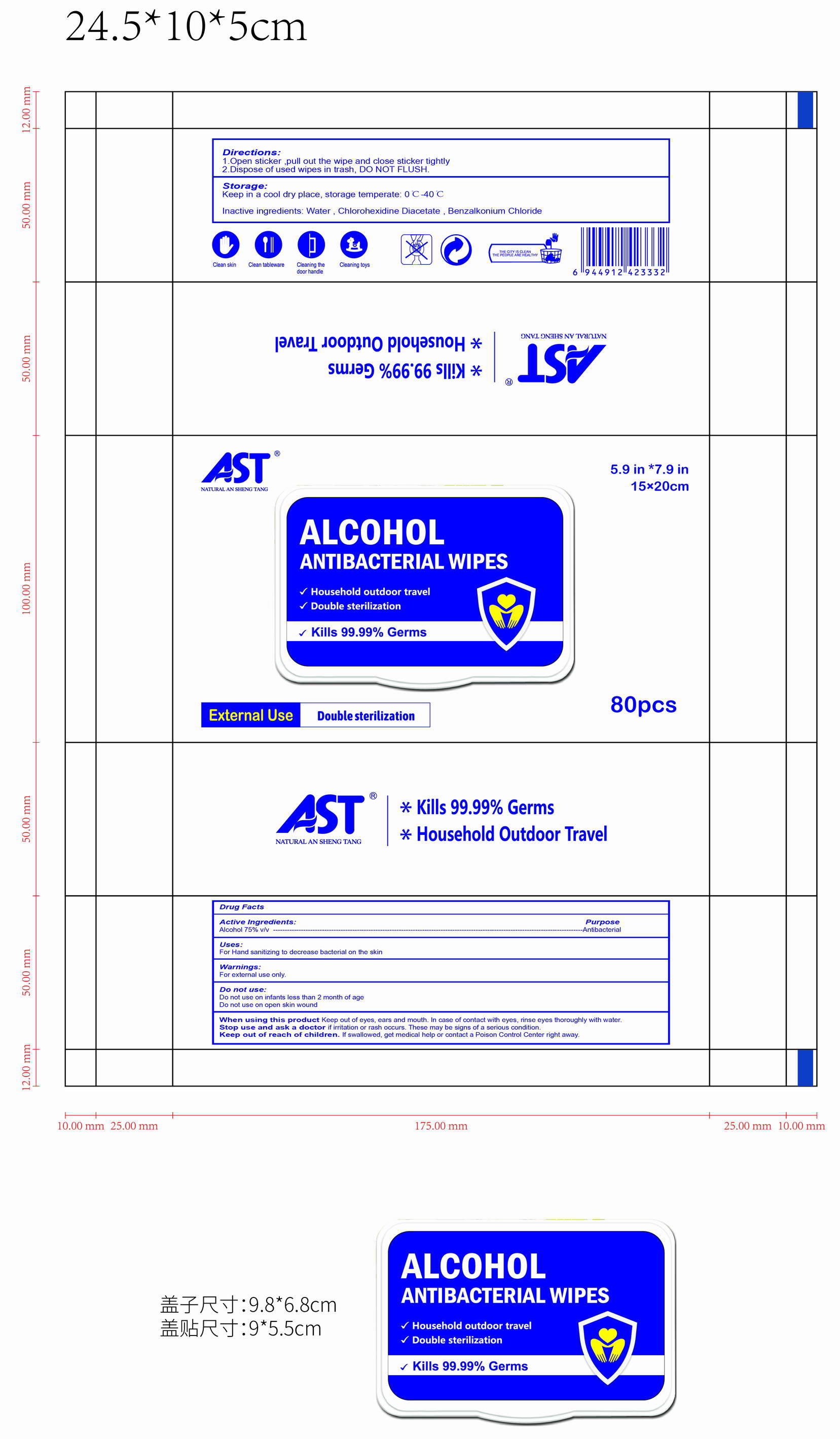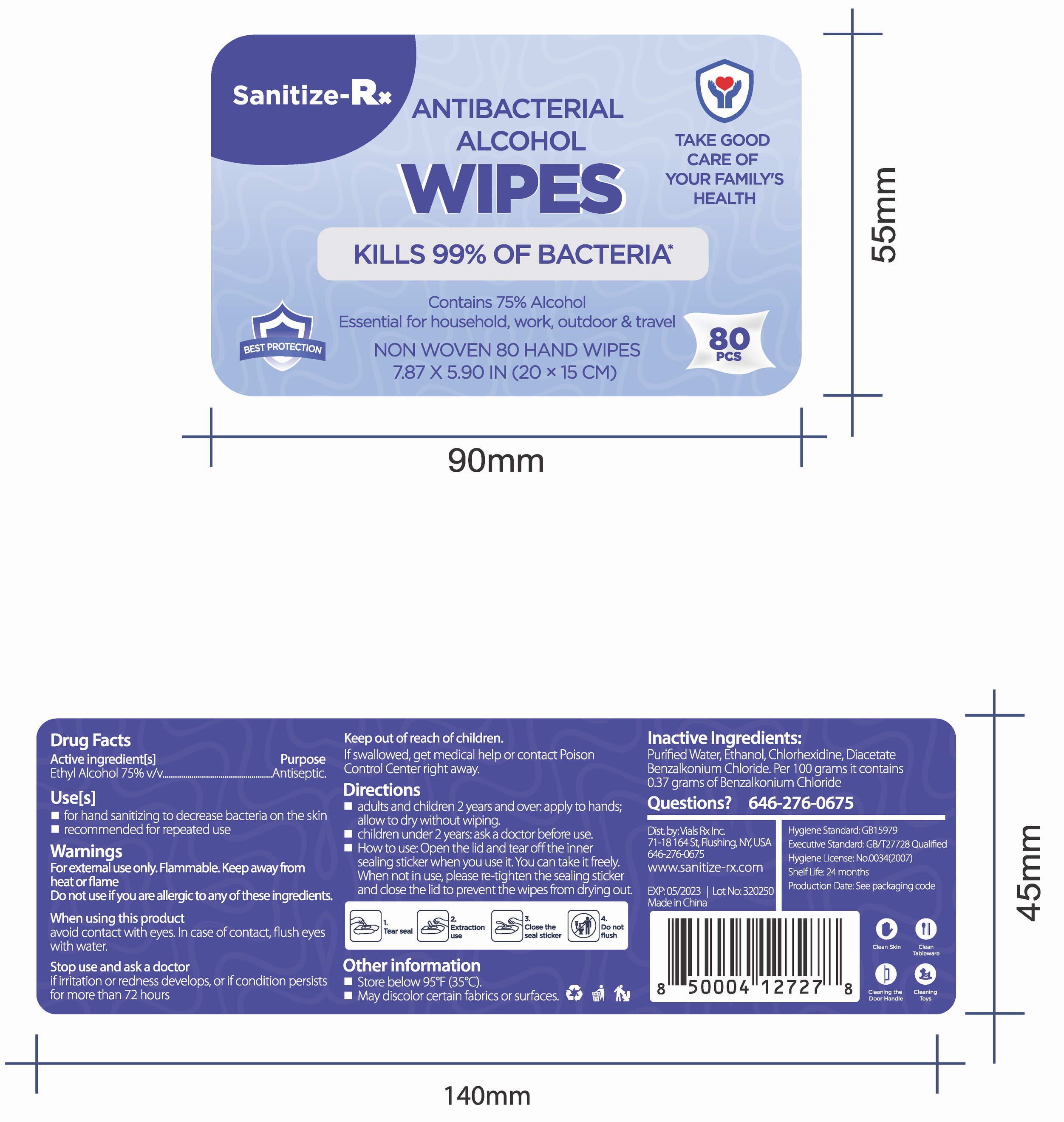 DRUG LABEL: Alcohol Antibacterial Wipes
NDC: 78183-001 | Form: CLOTH
Manufacturer: Kunming Ansheng Industry & Trade Co., Ltd.
Category: otc | Type: HUMAN OTC DRUG LABEL
Date: 20200701

ACTIVE INGREDIENTS: ALCOHOL 0.75 U/1 U
INACTIVE INGREDIENTS: CHLORHEXIDINE ACETATE 0.001 U/1 U; BENZALKONIUM CHLORIDE 0.001 U/1 U; WATER

AST Alcohol Antibacterial Wipes

Active Ingredient(s)

Alcohol 75% v/v;

Chlorohexidine Diacetate 0.1% v/v;

Benzalkonium 0.1% v/v;

Purpose

Antibacterial

Use

For hand sanitizing to decrease bacterial on the skin.

Warnings

For external use only. Flammable. Keep away from heat or flame

Do not use

- on infants less than 2 months of age
- on open skin wounds

When using this product keep out of eyes, ears, and mouth. In case of contact with eyes, rinse eyes thoroughly with water.

Stop use and ask a doctor if irritation or rash occurs. These may be signs of a serious condition.

Keep out of reach of children. If swallowed, get medical help or contact a Poison Control Center right away.

Directions

1, Open sticker, pull out the wipe and close sticker tightly.

2, Dispose of used wipes in trash, DO NOT FLUSH.

Other information

Keep in cool dry place, storage temperature: 0-40℃

Inactive ingredients

Inactive ingredients: Water, Chlorohexidine Diacetate, Benzalkonium Chloride

Package Label - Principal Display Panel

10 wipes in 1 bag. NDC: 78183-001-01;

20 wipes in 1 bag. NDC: 78183-001-02;

80 wipes in 1 bag. NDC: 78183-001-03;

100 wipes in 1 bag. NDC: 78183-001-04;

80 wipes in 1 bag. NDC: 78183-001-05;